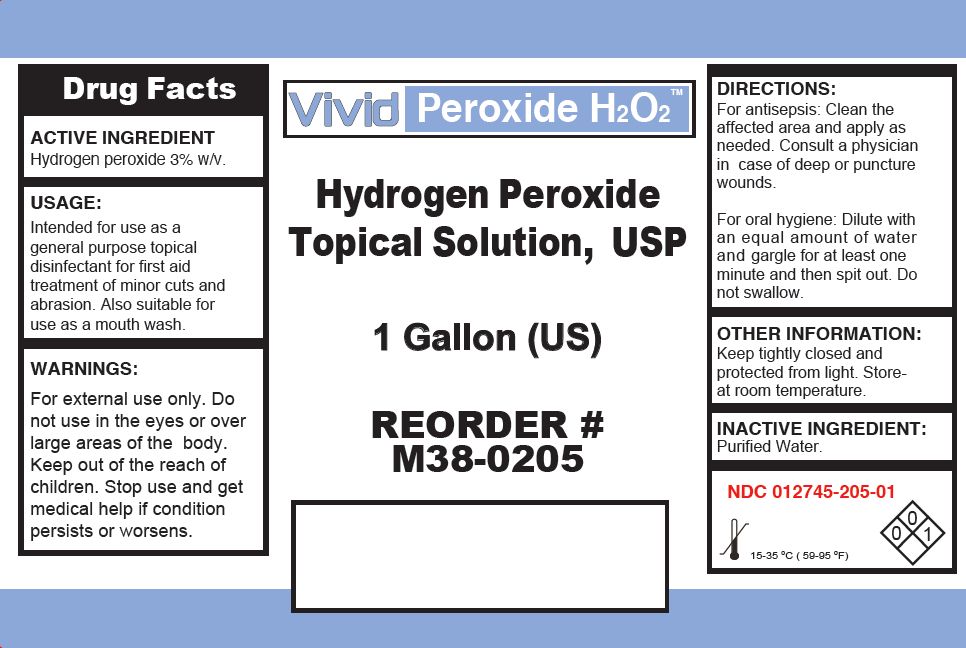 DRUG LABEL: HYDROGEN PEROXIDE
NDC: 12745-205 | Form: LIQUID
Manufacturer: Medical Chemical Corporation
Category: otc | Type: HUMAN OTC DRUG LABEL
Date: 20250828

ACTIVE INGREDIENTS: HYDROGEN PEROXIDE 8.57 g/100 mL
INACTIVE INGREDIENTS: WATER

Hydrogen Peroxide 3% Pearson Label

PURPOSE

Intended for use as a general purpose topical disinfectant for first aid treatment of minor cuts and abrasion. Also suitable for use as a mouth wash.

Active ingredient: hydrogen peroxide, 3% w/v

KEEP OUT OF REACH OF CHILDREN

For external use only.Do not use in the eyes or over large areas of the body. Keep out of the reach of children.Stop use and get medical help if condition persists or worsens.

INDICATIONS AND USAGE

Intended for use as a general purpose topical disinfectant for first aid treatment of minor cuts and abrasion. Also suitable for use as a mouth wash.

WARNINGS

For external use only. Do not use in the eyes or over large areas of the body. Keep out of the reachof children.Stop use and get medical help if condition persists or worsens.

DOSAGE AND ADMINISTRATION

For oral hygiene, dilute with an equal volume of water and gargle for about one minute. Rinse with water. In case of accidental ingestion contact a physician or a poison control center.

INACTIVE INGREDIENT

Purified Water.

PACKAGE LABEL

pearsonh2o2label.jpg